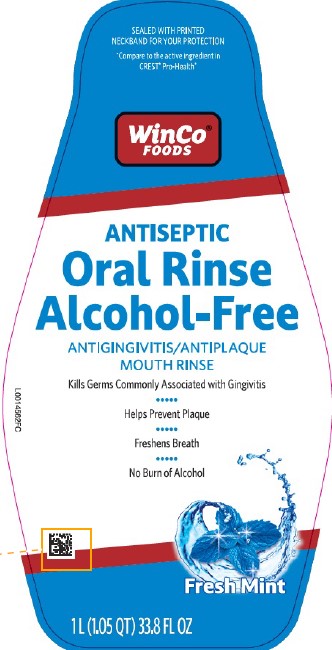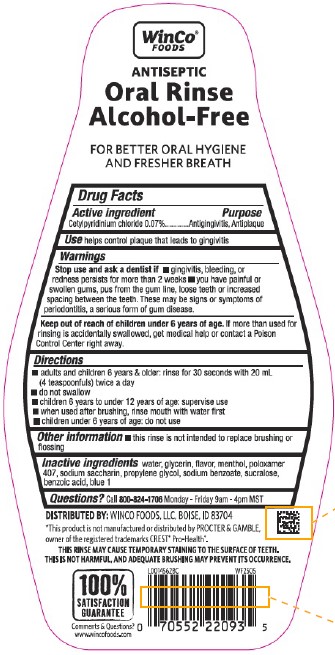 DRUG LABEL: Mint Alcohol Free
NDC: 67091-462 | Form: MOUTHWASH
Manufacturer: WinCo Foods LLC
Category: otc | Type: HUMAN OTC DRUG LABEL
Date: 20260212

ACTIVE INGREDIENTS: CETYLPYRIDINIUM CHLORIDE 0.7 mg/1 mL
INACTIVE INGREDIENTS: WATER; GLYCERIN; MENTHOL, UNSPECIFIED FORM; POLOXAMER 407; SACCHARIN SODIUM; PROPYLENE GLYCOL; SODIUM BENZOATE; SUCRALOSE; BENZOIC ACID; FD&C BLUE NO. 1

WinCo Foods 299.006/299AM
MULTI-ACTION ALCOHOL-FREE ANTISEPTIC MOUTH RINSE WITH CPC

Claims

WinCo®

ANTISEPTIC

Oral Rinse

Alcohol-Free

FOR BETTER ORAL HYGIENE AND FRESHER BREATH

ACTIVE INGREDIENT

Cetylpyridinium chloride 0.07%

PURPOSE

Antigingivitis, Antiplaque

Use

helps control plaque that leads to gingivitis

Warnings

for this product

Stop use and ask a dentist if

- gingivitis, bleeding, or redness persists for more than 2 weeks
- you have painful or swollen gums, pus from the gum line, loose teeth or increased spacing between the teeth. These may be signs or symptoms of periodontitis, a serious form of gum disease.

Keep out of reach of children under 6 years of age.

If more than used for rinsing is accidentally swallowed, get medical help or contact a Poison Control Center right away.

Directions

- adults and children 6 years & older: rinse for 30 seconds with 20 mL (4 teaspoonfuls) twice a day
- do not swallow
- children 6 years to under 12 years of age: supervise use
- when used after brushing, rinse mouth with water first
- children under 6 years of age: do not use

Other information

- this rinse is not intended to replace brushing or flossing

Inactive ingredients

water, glycerin, flavor, menthol, poloxamer 407, sodium saccharin, propylene glycol, sodium benzoate, sucralose, benzoic acid, blue 1

Questions?

Call 800-824-1706 Monday - Friday 9am - 4pm MST

ADVERSE REACTIONS SECTION

DISTRIBUTED BY: WINCO FOODS, LLC, BOISE, ID 83704

100% SATISFACTION GUARANTEE

Comments & Questions?

www.wincofoods.com

Disclaimers

*This product is not manufactured or distributed by PROCTER & GAMBLE, owner of the registered trademarks CREST®Pro-Health®.

THIS RINSE MAY CAUSE TEMPORARY STAINING TO THE SURFACE OF TEETH.

THIS IS NOT HARMFUL, AND ADEQUATE BRUSHING MAY PREVENT ITS OCCURRENCE.

PRINCIPAL DISPLAY PANEL

SEALED WITH PRINTED NECKBAND FOR YOUR PROTECTION

*Compare to the active ingredient in CREST®Pro-Health*

WinCo®

Foods

ANTISEPTIC

Oral Rinse

Alcohol-Free

ANTIGINGIVITIS/ANTIPLAQUE

MOUTH RINSE

Kills Germs Commonly Associated with Gingivitis

Helps Prevent Plaque

Freshens Breath

No Burn of Alcohol

Fresh Mint

1 L (1.05 QT) 33.8 FL OZ